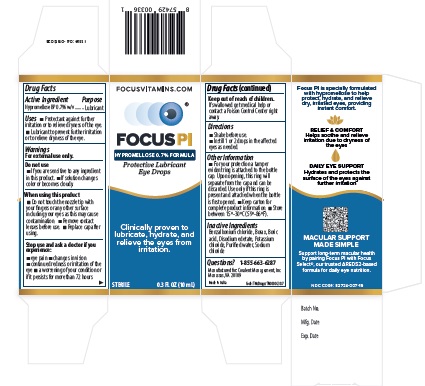 DRUG LABEL: Focus PI
NDC: 82724-007 | Form: FOR SOLUTION
Manufacturer: COVALENT MEDICAL
Category: otc | Type: HUMAN OTC DRUG LABEL
Date: 20260204

ACTIVE INGREDIENTS: HYPROMELLOSE 2910 (4000 MPA.S) 7 mg/1 mL
INACTIVE INGREDIENTS: BORIC ACID; WATER; BENZALKONIUM CHLORIDE; SODIUM BORATE; POTASSIUM CHLORIDE; EDETATE DISODIUM; SODIUM CHLORIDE

Focus PI

DIRECTIONS FOR USE

- lnstill 1or 2 drops in the affected eye, as needed

Active Ingredient

Hypromellose 0.7% BP w/v

INACTIVE INGREDIENT

1. Benzalkonium Chloride
2. Borax
3. Boric acid
4. EDTA disodium salt
5. Potassium chloride
6. Purified water
7. Sodiumchloride

Tamper Protection

- For your protection a tamper evident ring is attached to the bottlecap
- Upon opening, this will separate from the cap and can be discarded
- Use only if this ring is present and attached when the bottle is first opened

USE

- For use as a lubricant to prevent further irritation or to relieve dryness of the eye

Questions

Call: 855-663-6287
Email: Info@focusvitamins.com
Web: www.focusvitamins.com

KEEP OUT OF REACH OF CHILDREN

- If swallowed, get medical help or contact a poison control center right away

ASK DOCTOR

- If you experience eye pain
- Change in vision
- Continued redness(or) irritation of the eye
- Condition worsens or persists for more than 72 hours

DO NOT USE

- If you are sensitive to any ingredient in this product
- If solution changes color or becomes cloudy

Dosage

Instill 1 or 2 drops in the affected eyes as needed

Warnings

For External Use Only

Indications and Usage

For use as a lubricant to prevent further irritaion or to relieve dryness of the eye

Eye Lubricant